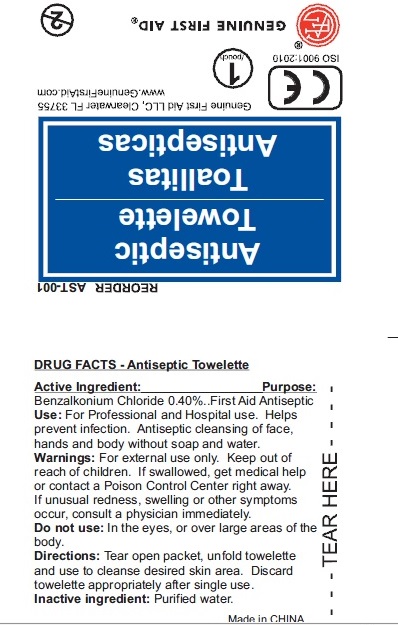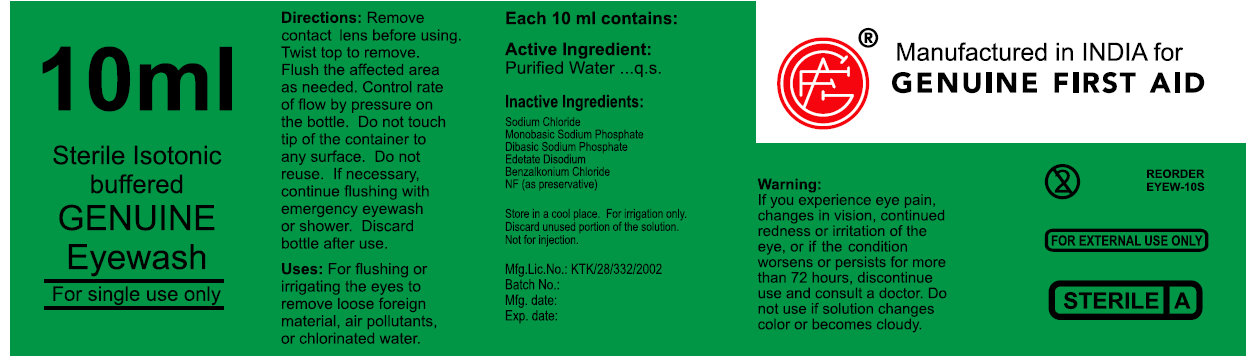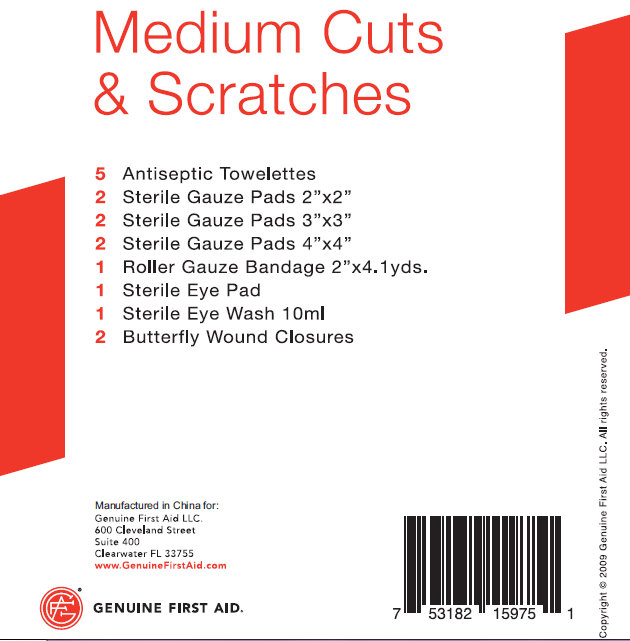 DRUG LABEL: Medium Cuts and Scratches
NDC: 52124-0117 | Form: KIT | Route: TOPICAL
Manufacturer: Genuine First Aid LLC
Category: otc | Type: HUMAN OTC DRUG LABEL
Date: 20100607

ACTIVE INGREDIENTS: BENZALKONIUM CHLORIDE 0.40 mL/100 mL; WATER 98.16 mL/100 mL
INACTIVE INGREDIENTS: WATER; SODIUM CHLORIDE; SODIUM PHOSPHATE, MONOBASIC; SODIUM PHOSPHATE, DIBASIC; EDETATE DISODIUM; BENZALKONIUM CHLORIDE

Medium Cuts & Scratches

Active Ingredient: Purpose

Benzalkonium Chloride 0.40%......First Aid Antiseptic

PURPOSE

Use: For Professional and Hospital use. Helps prevent infection. Antiseptic cleansing of face, hands and body without soap and water.

WARNINGS

Warning: For external use only.

Keep out of reach of children: If swallowed, get medical help or contact a Poison Control Center right away.

Stop use if unusual redness, swelling or other symptoms occur. Consult a physician immediately.

Do not use in the eyes or over large areas of the body.

WHEN USING

Directions: Tear open packet, unfold towelette and use to cleanse desired skin area. Discard towelette appropriately after single use.

Inactive Ingredient: Purified water

DESCRIPTION

LOT/EXP: Made in CHINA
20130301

PACKAGE LABEL

Antiseptic Towelette
Genuine First Aid LLC, Clearwater FL 33755
www.GenuineFirstAid.com
1/pouch
GENUINE FIRST AID

Active Ingredient:
Purified Water USP...q.s.

Inactive Ingredients:
Sodium Chloride USP 44mg
Monobasic Sodium Phosphate USP 18mg
Sodium Phosphate Dibasic USP 111mg
Edetate Disodium USP 10mg
Benzalkonium Chloride 0.5mg
NF (as preservative)

STORAGE AND HANDLING

Store in a cool place. For irrigation only.
Discard unused portion of the solution.
Not for injection.

Warning:
If you experience eye pain, changes in vision, continued redness or irritation of the eye,
or if the condition worsens or persists for more than 72 hours, discontinue use and consult a doctor.
Do not use if solution changes color or becomes cloudy.

Directions
Remove contacts before using.
Twist top to remove.
Flush the affected area as needed. Control
Rate of flow by pressure on the bottle. Do not touch
tip of the container to any surface. Do not reuse.
If necessary continue flushing with emergency eyewash or shower.
Discard bottle after use.

Uses:
For flushing or irrigating the eyes to
remove loose foreign material, air pollutants,
or chlorinated water.

DESCRIPTION

Code No.: GUJ/DRUG/G/1080
Batch No.:
Mfg Date:
Exp: Date:

PACKAGE LABEL

10ml
Sterile Isotonic Buffered Genuine
Eyewash
For single use only

PACKAGE LABEL

Medium Cuts, Burns and Severe Bleeding

5 Antiseptic Towelette
2 Sterile Gauge Pad 2"x2"
2 Sterile Gauge Pad 3"x3"
2 Sterile Gauge Pad 4"x4"
1 Roller Gauge Bandage 2"x4.1 yds.
1 Sterile Eye Pad
1 Sterile Eye Wash 10ml
2 Butterfly Wound Closures

Manufactured in China for:
Genuine First Aid LLC.
600 Cleveland Street
Suite 400
Clearwater FL 33755
www.GenuineFirstAid.com
GENUINE FIRST AID

Copyright 2009 Genuine First Aid LLC. All rights reserved.